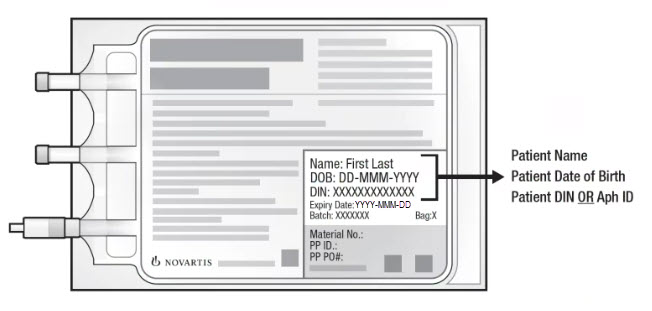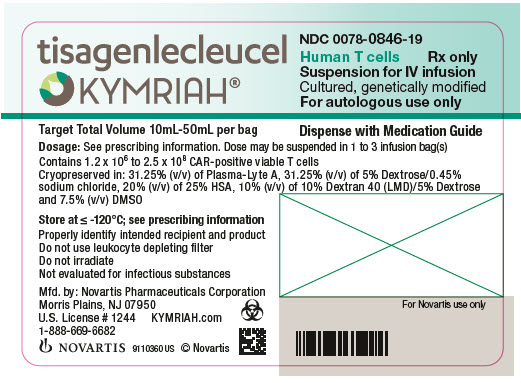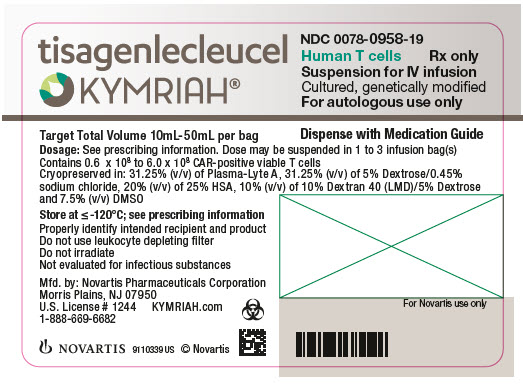 DRUG LABEL: KYMRIAH
NDC: 0078-0846 | Form: INJECTION, SUSPENSION
Manufacturer: Novartis Pharmaceuticals Corporation
Category: other | Type: CELLULAR THERAPY
Date: 20251216

ACTIVE INGREDIENTS: TISAGENLECLEUCEL 2000000 1/1 1
INACTIVE INGREDIENTS: DIMETHYL SULFOXIDE; ALBUMIN HUMAN; DEXTRAN 40

HIGHLIGHTS OF PRESCRIBING INFORMATION

These highlights do not include all the information needed to use KYMRIAH safely and effectively. See full prescribing information for KYMRIAH.
KYMRIAH® (tisagenlecleucel) suspension for intravenous infusion
Initial U.S. Approval: 2017

RECENT MAJOR CHANGES

Boxed Warning | 6/2025
Dosage and Administration (2.3) | 6/2025
Warnings and Precautions (5.1, 5.2, 5.4, 5.5, 5.6) | 12/2025
Warnings and Precautions, REMS (5.3) | Removed 6/2025

WARNING: CYTOKINE RELEASE SYNDROME, NEUROLOGICAL TOXICITIES, and SECONDARY HEMATOLOGICAL MALIGNANCIES

See full prescribing information for complete boxed warning.

- Cytokine Release Syndrome (CRS), including fatal or life-threatening reactions, occurred in patients receiving KYMRIAH. Do not administer KYMRIAH to patients with active infection or inflammatory disorders. Treat severe or life-threatening CRS with tocilizumab or tocilizumab and corticosteroids. (2.2, 2.3, 5.1)
- Neurological toxicities, including severe or life-threatening reactions, occurred following treatment with KYMRIAH, including concurrently with CRS. Monitor for neurological events after treatment with KYMRIAH. Provide supportive care and/or corticosteroids as needed. (5.2)
- T cell malignancies have occurred following treatment of hematologic malignancies with BCMA- and CD19- directed genetically modified autologous T cell immunotherapies, including KYMRIAH. (5.8)

1 INDICATIONS AND USAGE

KYMRIAH is a CD19-directed genetically modified autologous T cell immunotherapy indicated for the treatment of:

- Patients up to 25 years of age with B-cell precursor acute lymphoblastic leukemia (ALL) that is refractory or in second or later relapse. (1.1)
- Adult patients with relapsed or refractory (r/r) large B-cell lymphoma after two or more lines of systemic therapy, including diffuse large B-cell lymphoma (DLBCL) not otherwise specified, high grade B-cell lymphoma and DLBCL arising from follicular lymphoma.
  Limitations of Use: KYMRIAH is not indicated for treatment of patients with primary central nervous system lymphoma. (1.2)
- Adult patients with relapsed or refractory follicular lymphoma (FL) after two or more lines of systemic therapy. This indication is approved under accelerated approval based on response rate and duration of response. Continued approval for this indication may be contingent upon verification and description of clinical benefit in confirmatory trial(s). (1.3)

2 DOSAGE AND ADMINISTRATION

For autologous use only. For intravenous use only.

- Administer a lymphodepleting regimen if needed before infusion of KYMRIAH. (2.2)
- Do NOT use a leukodepleting filter. (2.2)
- Verify the patient’s identity prior to infusion. (2.2)
- Premedicate with acetaminophen and an H1-antihistamine. (2.2)
- Confirm availability of tocilizumab prior to infusion. (2.2, 5.1)
- Dosing of KYMRIAH is based on the number of chimeric antigen receptor (CAR)-positive viable T cells.
- Pediatric and Young Adult B-cell ALL (up to 25 years of age)
  • For patients 50 kg or less, administer 0.2 to 5.0 x 10^6 CAR-positive viable T cells per kg body weight intravenously. (2.1)
  • For patients above 50 kg, administer 0.1 to 2.5 x 10^8 total CAR-positive viable T cells (non-weight based) intravenously. (2.1)
- Adult Relapsed or Refractory Diffuse Large B-cell Lymphoma and Follicular Lymphoma
  • Administer 0.6 to 6.0 x 10^8 CAR-positive viable T cells intravenously. (2.1)

3 DOSAGE FORMS AND STRENGTHS

- Pediatric and Young Adult B-cell ALL (up to 25 years of age): A single dose of KYMRIAH contains 0.2 to 5.0 x 10^6 CAR-positive viable T cells per kg of body weight for patients 50 kg or less, or 0.1 to 2.5 x 10^8 CAR-positive viable T cells for patients more than 50 kg, suspended in one to three patient-specific infusion bag(s) for intravenous infusion. (3)
- Adult Relapsed or Refractory Diffuse Large B-cell Lymphoma and Follicular Lymphoma: A single dose of KYMRIAH contains 0.6 to 6.0 x 10^8 CAR-positive viable T cells suspended in one to three patient-specific infusion bag(s) for intravenous infusion. (3)

4 CONTRAINDICATIONS

None. (4)

5 WARNINGS AND PRECAUTIONS

- Hypersensitivity Reactions: Monitor for hypersensitivity reactions during infusion. (5.4)
- Serious Infections: Monitor patients for signs and symptoms of infection; treat appropriately. (5.5)
- Prolonged Cytopenias: Patients may exhibit ≥ Grade 3 cytopenias for several weeks following KYMRIAH infusion. Prolonged neutropenia has been associated with increased risk of infection. (5.6)
- Hypogammaglobulinemia: Monitor and provide replacement therapy until resolution. Assess immunoglobulin levels in newborns of mothers treated with KYMRIAH. (5.7)
- Secondary Malignancies: T cell malignancies have occurred following treatment of hematologic malignancies with BCMA- and CD19-directed genetically modified autologous T cell immunotherapies, including KYMRIAH. In the event that a secondary malignancy occurs after treatment with KYMRIAH, contact Novartis Pharmaceuticals Corporation at 1-844-4KYMRIAH. (5.8)

6 ADVERSE REACTIONS

Pediatric and Young Adult B-cell ALL (up to 25 years of age): The most common adverse reactions (incidence greater than 20%) are CRS, infections-pathogen unspecified, hypogammaglobulinemia, fever, decreased appetite, viral infectious disorders, headache, febrile neutropenia, hemorrhage, musculoskeletal pain, vomiting, encephalopathy, diarrhea, hypotension, cough, nausea, bacterial infectious disorders, pain, hypoxia, tachycardia, edema, fatigue, and acute kidney injury. (6.1)

Adult Relapsed or Refractory Diffuse Large B-cell Lymphoma: The most common adverse reactions (incidence greater than 20%) are CRS, infections-pathogen unspecified, fever, diarrhea, nausea, fatigue, hypotension, edema, hemorrhage, dyspnea, and headache. (6.1)

Adult Relapsed or Refractory Follicular Lymphoma: The most common adverse reactions (incidence greater than 20%) are CRS, infections-pathogens unspecified, fatigue, musculoskeletal pain, headache, and diarrhea. (6.1)

To report SUSPECTED ADVERSE REACTIONS, contact Novartis Pharmaceuticals Corporation at 1-888-669-6682 or FDA at 1-800-FDA-1088 or www.fda.gov/medwatch.

FULL PRESCRIBING INFORMATION

WARNING: CYTOKINE RELEASE SYNDROME, NEUROLOGICAL TOXICITIES, and SECONDARY HEMATOLOGICAL MALIGNANCIES

- Cytokine Release Syndrome (CRS), including fatal or life-threatening reactions, occurred in patients receiving KYMRIAH. Do not administer KYMRIAH to patients with active infection or inflammatory disorders. Treat severe or life-threatening CRS with tocilizumab or tocilizumab and corticosteroids [see Dosage and Administration (2.2, 2.3), Warnings and Precautions (5.1)].
- Neurological toxicities, including severe or life-threatening reactions, occurred following treatment with KYMRIAH, including concurrently with CRS. Monitor for neurological events after treatment with KYMRIAH. Provide supportive care and/or corticosteroids as needed [see Warnings and Precautions (5.2)].
- T cell malignancies have occurred following treatment of hematologic malignancies with BCMA- and CD19- directed genetically modified autologous T cell immunotherapies, including KYMRIAH [see Warnings and Precautions (5.8)].

1 INDICATIONS AND USAGE

1.1 Pediatric and Young Adult Relapsed or Refractory B-cell Acute Lymphoblastic Leukemia

KYMRIAH is indicated for treatment of patients up to 25 years of age with B-cell precursor acute lymphoblastic leukemia (ALL) that is refractory or in second or later relapse.

1.2 Adult Relapsed or Refractory Diffuse Large B-cell Lymphoma

KYMRIAH is indicated for treatment of adult patients with relapsed or refractory (r/r) large B-cell lymphoma after two or more lines of systemic therapy, including diffuse large B-cell lymphoma (DLBCL) not otherwise specified, high grade B-cell lymphoma and DLBCL arising from follicular lymphoma.

Limitation of Use: KYMRIAH is not indicated for treatment of patients with primary central nervous system lymphoma.

1.3 Adult Relapsed or Refractory Follicular Lymphoma

KYMRIAH is indicated for treatment of adult patients with relapsed or refractory (r/r) follicular lymphoma (FL) after two or more lines of systemic therapy.

This indication is approved under accelerated approval based on response rate and duration of response [see Clinical Studies (14.3)]. Continued approval for this indication may be contingent upon verification and description of clinical benefit in confirmatory trial(s).

2 DOSAGE AND ADMINISTRATION

2.1 Recommended Dose

For autologous use only. For intravenous use only.

Pediatric and Young Adult Relapsed or Refractory B-cell Acute Lymphoblastic Leukemia

KYMRIAH is provided as a single-dose for infusion containing a suspension of chimeric antigen receptor (CAR)-positive viable T cells.

Based on the patient weight reported at the time of leukapheresis:

- Patients 50 kg or less: administer 0.2 to 5.0 x 10^6 CAR-positive viable T cells per kg body weight.

- Patients above 50 kg: administer 0.1 to 2.5 x 10^8 CAR-positive viable T cells.

Adult Relapsed or Refractory Diffuse Large B-cell Lymphoma and Follicular Lymphoma

KYMRIAH is provided as a single-dose for infusion containing a suspension of chimeric antigen receptor (CAR)-positive viable T cells.

- For adult patients: administer 0.6 to 6.0 x 10^8 CAR-positive viable T cells.

2.2 Administration

Preparing Patient for KYMRIAH Administration with Lymphodepletion

- Confirm availability of KYMRIAH prior to starting the lymphodepleting regimen.

Pediatric and Young Adult Relapsed or Refractory B-cell Acute Lymphoblastic Leukemia

- Lymphodepleting chemotherapy: Fludarabine (30 mg/m^2 intravenously daily for 4 days) and cyclophosphamide (500 mg/m^2 intravenously daily for 2 days starting with the first dose of fludarabine).
- Infuse KYMRIAH 2 to 14 days after completion of the lymphodepleting chemotherapy.

Adult Relapsed or Refractory Diffuse Large B-cell Lymphoma and r/r Follicular Lymphoma

• Lymphodepleting chemotherapy: Fludarabine (25 mg/m^2 intravenously daily for 3 days) and cyclophosphamide (250 mg/m^2 intravenously daily for 3 days starting with the first dose of fludarabine).

• Alternate lymphodepleting chemotherapy: bendamustine 90 mg/m^2 intravenously daily for 2 days if a patient experienced a previous Grade 4 hemorrhagic cystitis with cyclophosphamide or demonstrates resistance to a previous cyclophosphamide containing regimen.

• Infuse KYMRIAH 2 to 11 days (r/r DLBCL) or 2 to 6 days (r/r FL) after completion of the lymphodepleting chemotherapy.

• Lymphodepleting chemotherapy may be omitted if a patient is experiencing significant cytopenia, e.g., white blood cell (WBC) count is less than 1 x 10^9/L within 1 week prior to KYMRIAH infusion.

Preparation of KYMRIAH for Infusion and Administration

Delay the infusion of KYMRIAH if a patient has unresolved serious adverse reactions (including pulmonary reactions, cardiac reactions, or hypotension) from preceding chemotherapies, active uncontrolled infection, active graft versus host disease (GVHD), or worsening of leukemia burden following lymphodepleting chemotherapy [see Warnings and Precautions (5.1)].

A KYMRIAH dose may be contained in one to three cryopreserved patient specific infusion bag(s). Verify the number of bags received for the dose of KYMRIAH with the Certificate of Conformance (CoC) and Certificate of Analysis (CoA). Coordinate the timing of thaw of KYMRIAH and infusion in the following manner. Confirm the infusion time in advance, and adjust the start time for thaw so that KYMRIAH is available for infusion when the recipient is ready. If more than one bag has been received for the treatment dose, thaw 1 bag at a time. Wait to thaw/infuse the next bag until it is determined that the previous bag is safely administered.

Preparation of KYMRIAH for Infusion

1. Confirm tocilizumab and emergency equipment are available prior to infusion and during the recovery period.

2. Premedicate patient with acetaminophen and diphenhydramine or another H1-antihistamine approximately 30 to 60 minutes prior to KYMRIAH infusion. Avoid prophylactic use of systemic corticosteroids, as it may interfere with the activity of KYMRIAH.

3. Confirm patient identity: Prior to KYMRIAH preparation, match the patient's identity with the patient identifiers on each KYMRIAH infusion bag(s). KYMRIAH is for autologous use only. Employ universal precautions to avoid potential transmission of infectious diseases when handling the product.

Note: The patient identifier number may be preceded by the letters DIN or Aph ID.

Figure 1. KYMRIAH Infusion Bag

4. Inspect the infusion bag(s) for any breaks or cracks prior to thawing. If a bag is compromised, do not infuse the contents. Call Novartis at 1-844-4KYMRIAH.

5. Place the infusion bag inside a second, sterile bag in case of a leak and to protect ports from contamination.

6. Thaw each infusion bag one at a time at 37°C using either a water bath or dry thaw method until there is no visible ice in the infusion bag. Remove bag from thawing device immediately; do not store product bag at 37°C. Once the infusion bag has been thawed and is at room temperature (20°C to 25°C), it should be infused within 30 minutes. Do not wash, spin down, and/or resuspend KYMRIAH in new media prior to infusion.

7. Inspect the contents of the thawed infusion bag for any visible cell clumps. If visible cell clumps remain, gently mix the contents of the bag. Small clumps of cellular material should disperse with gentle manual mixing. Do not infuse KYMRIAH if clumps are not dispersed, the infusion bag is damaged or leaking, or otherwise appears to be compromised. Call Novartis at 1-844-4KYMRIAH.

Administration of KYMRIAH

8. Confirm the patient’s identity with the patient identifiers on the infusion bag.

9. Administer KYMRIAH as an intravenous infusion at 10 mL to 20 mL per minute, adjusted as appropriate for smaller children and smaller volumes. The volume in the infusion bag ranges from 10 mL to 50 mL. Do NOT use a leukocyte-depleting filter. If more than one bag is being infused for the treatment dose, wait to thaw/infuse the next bag until it is determined that the previous bag is safely administered.

- Prime the tubing prior to infusion with sodium chloride 9 mg/mL (0.9%) solution for injection.

- Infuse all contents of the infusion bag.

- Rinse the infusion bag with 10 mL to 30 mL sodium chloride 9 mg/mL (0.9%) solution for injection while maintaining a closed tubing system to assure as many cells as possible are infused into the patient.

- Cells from all the bag(s) must be infused to complete a single dose.

KYMRIAH contains human cells genetically modified with a lentivirus. Follow local biosafety guidelines applicable for handling and disposal of such products.

Monitoring

- Monitor patients daily during the first week following KYMRIAH infusion for signs and symptoms of CRS and neurologic toxicities [see Warnings and Precautions (5.1, 5.2)].

- Instruct patients to remain within proximity of a healthcare facility for at least 2 weeks following infusion.

- Advise patients to avoid driving for at least 2 weeks following infusion.

2.3 Management of Severe Adverse Reactions

Cytokine Release Syndrome

Identify CRS based on clinical presentation [see Warnings and Precautions (5.1)]. Evaluate for and treat other causes of fever, hypoxia, and hypotension. If CRS is suspected, manage according to the recommendations in Table 1 (Lee et al., 2014). Alternative CRS management strategies may be implemented based on appropriate institutional or academic guidelines.

Table 1. CRS Grading and Management Guidance
CRS gradea | Symptomatic treatment | Tocilizumab | Corticosteroids
Grade 1 Mild symptoms requiring symptomatic treatment only (e.g., low grade fever, fatigue, anorexia, etc.) | Exclude other causes (e.g., infection) and treat specific symptoms (e.g., with antipyretics, antiemetics, analgesics, etc.) | In patients with persistent (> 3 days) or refractory fever, consider managing as Grade 2 CRSb. | Not applicable
Grade 2 Symptoms require and respond to moderate intervention Oxygen requirement < 40% or Hypotension responsive to fluids or low dose of one vasopressor or Grade 2 organ toxicity | Antipyretics, oxygen, intravenous fluids and/or low dose vasopressors as needed. | Administer tocilizumabc intravenously over 1 hour: - 8 mg/kg (max. 800 mg) if body weight ≥ 30 kg - 12 mg/kg if body weight < 30 kg If no improvement after first dose, repeat every 8 hours (limit to a maximum of 3 dosages in 24-hour period; maximum total of 4 doses). | If no improvement within 24 hours of tocilizumab, administer a daily dose of 2 mg/kg/day methylprednisolone intravenously (or equivalent) until vasopressor and oxygen no longer needed, then taper. If not improving, manage as appropriate grade below.
Grade 3 Symptoms require and respond to aggressive intervention Oxygen requirement ≥ 40% or Hypotension requiring high dose or multiple vasopressors or Grade 3 organ toxicity or Grade 4 transaminitis | High-flow oxygen Intravenous fluids, and high-dose or multiple vasopressors Treat other organ toxicities as per local guidelines. | Per Grade 2 If not improving, consider alternative therapyd. | Per Grade 2 If not improving, manage as Grade 4.
Grade 4 Life-threatening symptoms Requirement for ventilator support or Grade 4 organ toxicity (excluding transaminitis) | Mechanical ventilation Intravenous fluids and high-dose vasopressor(s) Treat other organ toxicities as per local guidelines. | Per Grade 2 If not improving, consider alternative therapyd. | Administer methylprednisolone 1,000 mg intravenously one to two times per day for 3 days. If not improving, consider methylprednisolone 1,000 mg intravenously two to three times a day or alternate therapyd. Continue corticosteroids until improvement to Grade 1, and then taper as clinically appropriate.
aLee et al., 2014.
bSantomasso et al., 2021.
cRefer to tocilizumab Prescribing Information for details.
dAlternative therapy includes anti-cytokine and anti-T cell therapies as per institutional policy and published guidelines such as (but not limited to) anakinra, siltuximab, ruxolitinib, cyclophosphamide, IVIG, and ATG.

Neurologic Toxicities

Patients should be monitored for neurologic toxicities, including ICANS, following KYMRIAH infusion, particularly during and after resolution of CRS. Identify neurologic toxicities based on clinical presentation. Evaluate for and treat other causes of neurological symptoms. Consider non-sedating seizure prophylaxis (e.g., levetiracetam) for patients at higher risk of seizure, such as those with seizure history, CNS disease, concerning EEG findings, or neoplastic brain lesions. If neurologic toxicity is suspected, manage according to the recommendations in Table 2. Alternative neurologic toxicities management strategies may be implemented based on appropriate institutional, academic, or consensus guidelines.

Table 2. Guidance for Grading and Management of ICANS
ICANS gradea | No concurrent CRS | Concurrent CRS
Grade 1 ICE scoreb: 7-9 with no depressed level of consciousness | Offer supportive care with intravenous hydration and aspiration precautions. | Administer tocilizumab at any grade CRS, as per dosage recommendation in Table 1. Caution with repeated tocilizumab doses in patients with ICANS. Consider adding corticosteroids to tocilizumab past the first dosec.
Grade 2 ICE scoreb: 3-6 and/or Mild somnolence awaking to voice | Supportive care as above. Consider dexamethasone 10 mg intravenously every 6-12 hours or methylprednisolone equivalent (1 mg/kg intravenously every 12 hours) until the event is Grade 1 or less. If improving, taper corticosteroids. | Administer tocilizumab at any grade CRS, as per dosage recommendation in Table 1. If refractory to tocilizumab past the first dose, administer dexamethasone 10 mg intravenously every 6-12 hours or methylprednisolone equivalent (1 mg/kg intravenously every 12 hours) until the event is Grade 1 or less, then taper corticosteroids.
Grade 3 ICE scoreb: 0-2* and/or Depressed level of consciousness awakening only to tactile stimulus and/or Any clinical seizure focal or generalized that resolves rapidly or nonconvulsive seizures on EEG that resolve with intervention and/or Focal or local edema on neuroimaging | Administer dexamethasone 10 mg intravenously every 6-12 hours or methylprednisolone equivalent (1 mg/kg intravenously every 12 hours). | Administer tocilizumab at any grade CRS, as per dosage recommendation in Table 1. Administer dexamethasone 10 mg intravenously every 6-12 hours or methylprednisolone equivalent (1 mg/kg intravenously every 12 hours). Continue corticosteroids until the event is Grade 1 or less, then taper corticosteroids. If not improving, manage as Grade 4.
Grade 4 ICE scoreb: 0* (patient is unarousable and unable to perform ICE) and/or Stupor or coma and/or Life-threatening prolonged seizure (> 5 minutes) or repetitive clinical or electrical seizures without return to baseline in between and/or Diffuse cerebral edema on neuroimaging, decerebrate or decorticate posturing or papilledema, cranial nerve VI palsy, or Cushing’s triad | Consider mechanical ventilation for airway protection. Administer high-dose methylprednisolone intravenously 1,000 mg one to two times per day for 3 days. If not improving, consider 1,000 mg of methylprednisolone two to three times per day or alternate therapyd. Continue corticosteroids until improvement to Grade 1, and then taper as clinically appropriate. Treat seizures, status epilepticus, and cerebral edema as per institutional guidelines. | Administer tocilizumab at any grade CRS, as per dosage recommendation in Table 1. Administer methylprednisolone 1,000 mg intravenously one to two times per day for 3 days. If not improving, consider methylprednisolone 1,000 mg intravenously two to three times per day or alternate therapyd. Continue corticosteroids until improvement to Grade 1, and then taper as clinically appropriate. Treat seizures, status epilepticus, and cerebral edema as per institutional guidelines.
aASTCT criteria for grading NT (Lee et al., 2019); NCI CTCAE criteria for grading NT used in clinical trials.
bICE Assessment Tool: (1) Orientation: orientation to year, month, city, and hospital: 4 points. (2) Naming: ability to name three objects (e.g., point to clock, pen, and button): 3 points. (3) Following commands: ability to follow simple commands (e.g., show me 2 fingers or close your eyes and stick out your tongue): 1 point. (4) Writing: ability to write a standard sentence (e.g., Our national bird is the bald eagle): 1 point. (5) Attention: ability to count backward from 100 by 10: 1 point.
cSantomasso et. al., 2021.
dAlternate therapy may include anakinra, siltuximab, ruxolitinib, cyclophosphamide, antithymocyte globulin, or intrathecal hydrocortisone (50 mg) plus methotrexate (12 mg).
*A patient with an ICE score of 0 may be classified as Grade 3 ICANS if awake with global aphasia, but a patient with an ICE score of 0 may be classified as Grade 4 ICANS if unarousable.

3 DOSAGE FORMS AND STRENGTHS

Pediatric and Young Adult r/r B-cell ALL (up to 25 years of age): A single dose of KYMRIAH contains 0.2 to 5.0 x 10^6 CAR-positive viable T cells per kg of body weight for patients 50 kg and below or 0.1 to 2.5 x 10^8 CAR-positive viable T cells for patients above 50 kg, suspended in one to three patient-specific infusion bag(s) [see How Supplied/Storage and Handling (16)].

Adult r/r DLBCL and r/r FL: A single dose of KYMRIAH contains 0.6 to 6.0 x 10^8 CAR-positive viable T cells, which may be suspended in one to three patient-specific infusion bag(s) [see How Supplied/Storage and Handling (16)].

See the CoA for actual cell count. The volume in the infusion bag ranges from 10 mL to 50 mL.

4 CONTRAINDICATIONS

None.

5 WARNINGS AND PRECAUTIONS

5.1 Cytokine Release Syndrome

Cytokine release syndrome (CRS), including fatal or life-threatening reactions, occurred following treatment with KYMRIAH. CRS occurred in 61 (77%) of the 79 pediatric and young adult patients with r/r ALL receiving KYMRIAH, including ≥ Grade 3 CRS (Penn grading system^1) occurring in 48% of patients. The median times to onset and resolution of CRS were 3 days (range, 1 to 22; 1 patient with onset after Day 10) and 8 days (range, 1 to 36), respectively. Of the 61 patients with CRS, 31 (51%) received tocilizumab. Ten (16%) patients received two doses of tocilizumab and 3 (5%) patients received three doses of tocilizumab; 17 (28%) patients received addition of corticosteroids (e.g., methylprednisolone).

CRS occurred in 85 (74%) of the 115 adult patients with r/r DLBCL receiving KYMRIAH, including ≥ Grade 3 CRS (Penn grading system^1) occurring in 23% of patients. The median times to onset and resolution of CRS were 3 days (range, 1 to 51; 1 patient with onset after Day 10) and 7 days (range, 2 to 30), respectively. Of the 85 patients with CRS, 19 (22%) received systemic tocilizumab or corticosteroids. Seven (8%) patients received a single dose of tocilizumab and 11 (13%) patients received two doses of tocilizumab; 11 (13%) patients received corticosteroids in addition to tocilizumab. One patient received corticosteroids for CRS without concomitant tocilizumab, and two patients received corticosteroids for persistent neurotoxicity after resolution of CRS.

CRS occurred in 51 (53%) of the 97 adult patients with r/r FL receiving KYMRIAH; all were Grade 1 or 2 CRS (Lee grading system^2). The median times to onset and resolution of CRS were 4 days (range, 1 to 14) and 4 days (range, 1 to 13), respectively. Of the 51 patients with CRS, 15 (29%) received systemic anticytokine treatment with tocilizumab. Three (6%) patients required 3 dosages of tocilizumab, 4 (8%) patients required 2 dosages and 8 (16%) patients required single dose of tocilizumab. Two (4%) patients received corticosteroids in addition to tocilizumab.

Five deaths occurred within 30 days of KYMRIAH infusion. One patient with r/r ALL died with CRS and progressive leukemia, and one patient had resolving CRS with abdominal compartment syndrome, coagulopathy, and renal failure when an intracranial hemorrhage occurred. Of the 3 r/r DLBCL patients who died within 30 days of infusion, all had CRS in the setting of stable to progressive underlying disease, one of whom developed bowel necrosis.

Among patients with CRS, key manifestations include fever (93% in r/r ALL; 85% in r/r DLBCL; 92% in r/r FL), hypotension (69% in r/r ALL; 45% in r/r DLBCL; 40% in r/r FL), hypoxia (57% in r/r ALL; 35% in r/r DLBCL; 19% in r/r FL), and tachycardia (26% in r/r ALL; 13% in r/r DLBCL; 2% in r/r FL). CRS may be associated with hepatic, renal, and cardiac dysfunction, and coagulopathy.

Delay the infusion of KYMRIAH after lymphodepleting chemotherapy if the patient has unresolved serious adverse reactions from preceding chemotherapies (including pulmonary toxicity, cardiac toxicity, or hypotension), active uncontrolled infection, active graft versus host disease (GVHD), or worsening of leukemia burden [see Dosage and Administration (2.2)].

Risk factors for severe CRS in the pediatric and young adult r/r B-cell ALL population are high pre-infusion tumor burden (greater than 50% blasts in bone marrow), uncontrolled or accelerating tumor burden following lymphodepleting chemotherapy, active infections, and/or inflammatory processes.

Confirm that a minimum of two doses of tocilizumab are available on site prior to infusion of KYMRIAH.

Monitor patients daily during the first week following KYMRIAH infusion for signs and symptoms of CRS. Monitor patients for signs or symptoms of CRS for at least 2 weeks after treatment with KYMRIAH. At the first sign of CRS, immediately evaluate patient for hospitalization and institute treatment with supportive care, tocilizumab and/or corticosteroids as indicated [see Dosage and Administration (2.2, 2.3)].

Counsel patients to seek immediate medical attention should signs or symptoms of CRS occur at any time [see Patient Counseling Information (17)].

5.2 Neurological Toxicities

Neurological toxicities, including severe or life-threatening reactions, occurred following treatment with KYMRIAH. Neurologic toxicities occurred in 56 (71%) of the 79 patients with r/r ALL, including ≥ Grade 3 in 22%. The median times to the first event and duration were 6 days from infusion (range, 1 to 301) and 7 days, respectively.

Neurologic toxicities occurred in 69 (60%) of the 115 patients with r/r DLBCL, including ≥ Grade 3 in 19%. The median times to the first event and duration were 5 days (range, 1 to 368) and 17 days, respectively.

Neurologic toxicities occurred in 42 (43%) of the 97 patients with r/r FL, including ≥ Grade 3 in 6%. The median times to the first event and duration were 8 days (range, 1 to 345) and 5 days, respectively.

Among patients who had a neurological toxicity, 84% occurred within 8 weeks following KYMRIAH infusion. Resolution occurred within 3 weeks in 71% of patients with r/r ALL, 50% of patients with r/r DLBCL, and 74% of patients with r/r FL. Encephalopathy lasting up to 70 days was noted.

The onset of neurological toxicity can be concurrent with CRS, following resolution of CRS or in the absence of CRS.

The most common neurological toxicities observed with KYMRIAH include headache (35% in r/r ALL; 21% in r/r DLBCL; 25% in r/r FL), encephalopathy (30% in r/r ALL; 16% in r/r DLBCL; 3% in r/r FL), delirium (19% in r/r ALL; 5% in r/r DLBCL; 1% in r/r FL), anxiety (16% in r/r ALL; 10% in r/r DLBCL; 2% in r/r FL), sleep disorders (11% in r/r ALL; 10% in r/r DLBCL; 6% in r/r FL), dizziness (5% in r/r ALL; 12% in r/r DLBCL; 8% in r/r FL), tremor (8% in r/r ALL; 6% in r/r DLBCL; 3% in r/r FL), and peripheral neuropathy (4% in r/r ALL; 12% in r/r DLBCL; 7% in r/r FL). Other manifestations included seizures and aphasia.

Monitor patients daily during the first week following KYMRIAH infusion for signs and symptoms of neurologic toxicities. Rule out other causes of neurological symptoms. Monitor patients for signs or symptoms of neurologic toxicities for at least 2 weeks after infusion and treat promptly. Neurologic toxicity should be managed with supportive care and/or corticosteroids as needed [see Dosage and Administration (2.3)]. Advise patients to avoid driving for at least 2 weeks following infusion.

Counsel patients to seek immediate medical attention should signs or symptoms of neurologic toxicity occur at any time [see Patient Counseling Information (17)].

5.3 Hemophagocytic Lymphohistiocytosis/Macrophage Activation Syndrome

Hemophagocytic Lymphohistiocytosis (HLH)/Macrophage Activation Syndrome (MAS), which can be life-threatening or fatal, has occurred following treatment with KYMRIAH. HLH was reported in 6% (5/79) of patients with r/r ALL (time to onset ranged from 3 to 18 days) and 2% (2/115) of patients with r/r DLBCL (times to onset were Day 7 and Day 10); all HLH events occurred during ongoing CRS and resolved. One patient (1%) with r/r FL developed HLH > 1 year after receiving KYMRIAH with a fatal outcome. The patient did not have CRS during or immediately preceding HLH. Treatment of HLH should be administered as per institutional standards.

5.4 Hypersensitivity Reactions

Hypersensitivity reactions may occur with infusion of KYMRIAH. Serious hypersensitivity reactions, including anaphylaxis, may be due to the dimethyl sulfoxide (DMSO) or dextran 40 in KYMRIAH. Observe patients for hypersensitivity reactions during and after the infusion.

5.5 Serious Infections

Infections, including life-threatening or fatal infections, occurred following treatment with KYMRIAH. Infections occurred in 57 (72%) of the 79 patients with r/r ALL; 38 patients (48%) experienced ≥ Grade 3 infections, including fatal infections in 2 patients (3%).

Infections occurred in 67 (58%) of the 115 patients with r/r DLBCL; 38 patients (33%) experienced ≥ Grade 3 infections, including fatal infection in 1 patient (1%).

Infections occurred in 50 (52%) of the 97 patients with r/r FL; 20 patients (21%) experienced ≥ Grade 3 infections, including fatal infection in 1 patient (1%).

Prior to KYMRIAH infusion, infection prophylaxis should follow local guidelines. Patients with active uncontrolled infection should not start KYMRIAH treatment until the infection is resolved. Monitor patients for signs and symptoms of infection after treatment with KYMRIAH and treat appropriately [see Dosage and Administration (2.2)].

Febrile neutropenia (≥ Grade 3) was also observed in 34% of patients with r/r ALL, 17% of patients with r/r DLBCL, and 13% of patients with r/r FL after KYMRIAH infusion and may be concurrent with CRS. In the event of febrile neutropenia, evaluate for infection and manage with broad spectrum antibiotics, fluids and other supportive care as medically indicated.

In immunosuppressed patients, opportunistic fatal infections of the central nervous system including progressive multifocal leukoencephalopathy due to John Cunningham virus reactivation have occurred after KYMRIAH administration [see Clinical Trial Experience (6.1) and Postmarketing Experience (6.2)]. Perform appropriate diagnostic evaluations in patients with neurological adverse events.

Viral Reactivation

Hepatitis B virus (HBV) reactivation, in some cases resulting in fulminant hepatitis, hepatic failure and death, can occur in patients treated with drugs directed against B cells.

There is no experience with manufacturing KYMRIAH for patients with a positive test for HIV or with active HBV or active HCV. Perform screening for HBV, HCV, and HIV in accordance with clinical guidelines before collection of cells for manufacturing.

5.6 Prolonged Cytopenias

Patients may exhibit cytopenias for several weeks following lymphodepleting chemotherapy and KYMRIAH infusion.

In Study 1, ≥ Grade 3 cytopenias not resolved by Day 28 following KYMRIAH treatment included neutropenia (40%), and thrombocytopenia (27%) among 52 responding patients. At 56 days following KYMRIAH, 17% and 12% of responding patients had ≥ Grade 3 neutropenia or thrombocytopenia, respectively.

In Study 2, ≥ Grade 3 cytopenias not resolved by Day 28 following KYMRIAH treatment included thrombocytopenia (39%) and neutropenia (25%) among 115 treated patients.

In Study 3, ≥ Grade 3 cytopenias not resolved by Day 28 following KYMRIAH treatment included thrombocytopenia (17%) and neutropenia (16%) among 97 treated patients.

Prolonged neutropenia has been associated with increased risk of infection. Myeloid growth factors, particularly GM-CSF, are not recommended during the first 3 weeks after KYMRIAH infusion or until CRS has resolved.

5.7 Hypogammaglobulinemia

Hypogammaglobulinemia and agammaglobulinemia related to B-cell aplasia can occur in patients after KYMRIAH infusion.

Hypogammaglobulinemia was reported in 53% of patients treated with KYMRIAH for r/r ALL, 17% of patients with r/r DLBCL, and 18% of patients with r/r FL [see Clinical Pharmacology (12.3)].

Monitor immunoglobulin levels after treatment with KYMRIAH and manage using infection precautions, antibiotic prophylaxis, and immunoglobulin replacement standard guidelines.

Immunization with Live Vaccine

The safety of immunization with live vaccines during or following KYMRIAH treatment has not been studied. Vaccination with live vaccines is not recommended for at least 6 weeks prior to the start of lymphodepleting chemotherapy, during KYMRIAH treatment, and until immune recovery following treatment with KYMRIAH.

Pregnant women who have received KYMRIAH may have hypogammaglobulinemia. Assess immunoglobulin levels in newborns of mothers treated with KYMRIAH.

5.8 Secondary Malignancies

Patients treated with KYMRIAH may develop secondary malignancies or recurrence of their cancer. T cell malignancies have occurred following treatment of hematologic malignancies with BCMA- and CD19- directed genetically modified autologous T cell immunotherapies, including KYMRIAH. Mature T cell malignancies, including CAR-positive tumors, may present as soon as weeks following infusion, and may include fatal outcomes [see Boxed Warning, Adverse Reactions (6.2), Patient Counseling Information (17)].

Monitor life-long for secondary malignancies. In the event that a secondary malignancy occurs, contact Novartis Pharmaceuticals Corporation at 1-844-4KYMRIAH to obtain instructions on patient samples to collect for testing.

6 ADVERSE REACTIONS

6.1 Clinical Trials Experience

Because clinical trials are conducted under widely varying conditions, adverse reaction rates observed in the clinical trials of a drug cannot be directly compared to rates in the clinical trials of another drug and may not reflect the rates observed in practice.

The safety data described in the WARNINGS AND PRECAUTIONS and in this section reflect exposure to KYMRIAH in three non-randomized, single-arm studies in which 79 pediatric and young adult patients with relapsed/refractory (r/r) B-cell ALL (Study 1: CCTL019B2202), 115 adults with r/r diffuse large B-cell lymphoma (Study 2: CCTL019C2201), and 97 adults with r/r follicular lymphoma (Study 3: CCTL019E2202) received a single dose of CAR-positive viable T cells.

Pediatric and Young Adult r/r B-cell Acute Lymphoblastic Leukemia (ALL) (up to 25 years of age)

Based on a recommended dose which was weight-based, all 79 patients in the Study 1 received a single intravenous dose of KYMRIAH [see Clinical Studies (14.1)]. The most common adverse reactions (> 20%) were CRS (77%), infections-pathogen unspecified (57%), hypogammaglobulinemia (53%), fever (42%), decreased appetite (38%), viral infectious disorders (38%), headache (35%), febrile neutropenia (34%), hemorrhage (32%), musculoskeletal pain (32%), vomiting (32%), encephalopathy (30%), bacterial infectious disorders (29%), diarrhea (29%), hypotension (29%), cough (27%), nausea (27%), pain (25%), hypoxia (25%), tachycardia (24%), edema (23%), fatigue (23%), and acute kidney injury (22%).

The adverse reactions with greater than or equal to 10% incidence for any Grade are summarized in Table 3.

Table 3. Adverse Reactions in ≥ 10% of Pediatric and Young Adults Patients with r/r B-cell ALL in Study 1 (N = 79)
Adverse reaction | All Grades (%) | Grades 3 or higher (%)
Blood and lymphatic system disorders
Febrile neutropenia | 34 | 34
Cardiac disorders
Tachycardiaa | 24 | 4
Gastrointestinal disorders
Vomiting | 32 | 1
Diarrhea | 29 | 1
Nausea | 27 | 3
Abdominal paina | 18 | 3
Constipation | 18 | 0
General disorders and administration site conditions
Fever | 42 | 13
Paina | 25 | 3
Fatiguea | 23 | 0
Edemaa | 23 | 8
Immune system disorders
Cytokine release syndrome | 77 | 48
Hypogammaglobulinemiaa | 53 | 13
Infections and infestations
Infections-pathogen unspecified | 57 | 27
Viral infectious disorders | 37 | 22
Bacterial infectious disorders | 29 | 16
Fungal infectious disorders | 15 | 9
Metabolism and nutrition disorders
Decreased appetite | 38 | 15
Hypocalcemia | 20 | 6
Hyperferritinemiaa | 10 | 3
Musculoskeletal and connective tissue disorders
Musculoskeletal paina | 32 | 4
Arthralgia | 14 | 1
Nervous system disorders
Headachea | 35 | 3
Encephalopathyb | 30 | 9
Psychiatric disorders
Deliriuma | 19 | 4
Anxiety | 17 | 3
Sleep disordera | 11 | 0
Renal and urinary disorders
Acute kidney injurya | 22 | 14
Respiratory, thoracic and mediastinal disorders
Cougha | 27 | 0
Hypoxia | 25 | 20
Dyspneac | 19 | 14
Pulmonary edema | 15 | 9
Nasal congestion | 11 | 0
Oropharyngeal pain | 10 | 0
Pleural effusion | 10 | 4
Tachypnea | 10 | 5
Skin and subcutaneous tissue disorders
Rasha | 18 | 1
Vascular disorders
Hemorrhagea | 32 | 10
Hypotension | 29 | 20
Hypertension | 19 | 5
aIncludes multiple related composite terms.
bEncephalopathy includes encephalopathy, cognitive disorder, confusional state, depressed level of consciousness, disturbance in attention, lethargy, mental status changes, somnolence, memory impairment, and automatism. Encephalopathy is a dominant feature of immune effector cell-associated neurotoxicity syndrome (ICANS), along with other symptoms.
cDyspnea includes acute respiratory failure, dyspnea, respiratory distress, and respiratory failure.

Other clinically important adverse reactions which occurred in <10% of patients include the following:

Blood and lymphatic system disorders: coagulopathy (6%), hemophagocytic lymphohistiocytosis (6%), pancytopenia (3%)

Cardiac disorders: cardiac failure (9%), arrhythmia (4%)

Eye disorders: visual impairment (3%)

Gastrointestinal disorders: abdominal distention (4%), ascites (4%), stomatitis (4%), abdominal compartment syndrome (1%), dry mouth (1%)

General disorders and administration site conditions: chills (9%), asthenia (4%), influenza-like illness (3%), multiple organ dysfunction syndrome (3%)

Immune system disorders: infusion related reaction (6%), graft versus host disease (3%)

Investigations: prothrombin time prolonged (4%), fibrin D dimer increased (3%), weight decreased (3%)

Metabolism and nutrition disorders: tumor lysis syndrome (6%), hypercalcemia (4%)

Nervous system disorders: tremor (8%), seizure (6%), dizziness (5%), peripheral neuropathy (4%), speech disorder (3%), motor dysfunction (1%), neuralgia (1%)

Respiratory, thoracic, and mediastinal disorders: acute respiratory distress syndrome (4%), lung infiltration (1%)

Skin and subcutaneous tissue disorders: pruritus (9%), erythema (6%), hyperhidrosis (4%), night sweats (1%)

Vascular disorders: capillary leak syndrome (3%), thrombosis (3%), flushing (1%)

Laboratory Abnormalities

Table 4. Grade 3 or 4 Laboratory Abnormalities Occurring in > 10% of Pediatric and Young Adult Patients with r/r B-cell ALL in Study 1 (N = 79)
Laboratory abnormality | Grade 3 or 4a (%)
Hematology
Blood fibrinogen decreased | 11
Biochemistry
Aspartate aminotransferase increased | 29
Hypokalemia | 28
Alanine aminotransferase increased | 22
Hypophosphatemia | 20
Hyperbilirubinemia | 19
Hyperglycemia | 13
aCTCAE = Common Terminology Criteria for Adverse Events version 4.03.

All patients experienced neutropenia, anemia and thrombocytopenia. See Table 5 for the incidences of ≥ Grade 3 prolonged thrombocytopenia and prolonged neutropenia in responding patients.

Table 5. Prolonged Cytopenias Following Treatment with KYMRIAH in Pediatric and Young Adult r/r B-cell ALL
Prolonged cytopenia | N = 52 (%) | N = 52 (%)
 | Day 28 | Day 56
Prolonged neutropeniaa | 40 | 17
Prolonged thrombocytopeniaa | 27 | 12
a≥ Grade 3 observed within 14 days after Day 28 or Day 56 in responding patients.

Adult r/r Diffuse Large B-cell Lymphoma (DLBCL)

In Study 2, 115 adults with r/r DLBCL received a single intravenous dose of KYMRIAH [see Clinical Studies (14.2)]. The most common adverse reactions (incidence > 20%) were CRS, infections-pathogen unspecified, fever, diarrhea, nausea, fatigue, hypotension, edema, bleeding episodes, dyspnea, and headache.

The study population characteristics were median age of 56 years (range, 22 to 76 years), 80% DLBCL; a median of 3 prior lines of therapy (range, 1 to 6), 49% had a prior autologous hematopoietic stem cell transplantation, and 32% had received prior radiation therapy. One hundred seven patients (93%) received lymphodepleting chemotherapy prior to KYMRIAH, which included fludarabine (n = 85) or bendamustine (n = 22).

The adverse reactions with greater than or equal to 10% incidence for any Grade are summarized in Table 6 below.

Table 6. Adverse Reactions Reported in ≥ 10% of Adult Patients with r/r DLBCL in Study 2 (N = 115)
Adverse reaction | All Grades (%) | Grades 3 or higher (%)
Blood and lymphatic system disorders
Febrile neutropenia | 17 | 17
Cardiac disorders
Tachycardiaa | 13 | 3
Arrhythmiaa | 10 | 5
Gastrointestinal disorders
Diarrhea | 31 | 1
Nausea | 29 | 1
Constipation | 17 | 1
Abdominal paina | 10 | 2
General disorders and administration site conditions
Fever | 35 | 5
Fatiguea | 27 | 6
Edemaa | 27 | 3
Paina | 14 | 3
Chills | 12 | 0
Immune system disorders
Cytokine release syndrome | 74 | 23
Hypogammaglobulinemiaa | 17 | 6
Infections and infestations
Infections-pathogen unspecified | 48 | 26
Bacterial infectious disorders | 17 | 8
Fungal infectious disorders | 11 | 5
Viral infectious disorders | 11 | 2
Investigations
Weight decreased | 12 | 4
Metabolism and nutrition disorders
Decreased appetite | 14 | 4
Musculoskeletal and connective tissue disorders
Arthralgia | 14 | 0
Musculoskeletal paina | 13 | 1
Nervous system disorders
Headachea | 21 | 1
Encephalopathyb | 16 | 11
Peripheral neuropathyc | 12 | 3
Dizzinessd | 12 | 2
Psychiatric disorders
Anxiety | 10 | 1
Sleep disordera | 10 | 0
Renal and urinary disorders
Acute kidney injurya | 17 | 6
Respiratory, thoracic and mediastinal disorders
Dyspneae | 21 | 6
Cougha | 17 | 0
Skin and subcutaneous tissue disorders
Rasha | 11 | 0
Vascular disorders
Hypotensiona | 25 | 9
Hemorrhagea | 22 | 8
aIncludes multiple related composite terms.
bEncephalopathy includes cognitive disorder, confusional state, disturbance in attention, lethargy, mental status changes, somnolence, memory impairment, metabolic encephalopathy and thinking abnormal. Encephalopathy is a dominant feature of immune effector cell-associated neurotoxicity syndrome (ICANS), along with other symptoms.
cPeripheral neuropathy includes paraesthesia, hypoaesthesia, hyperaesthesia, peripheral sensory neuropathy, neuropathy peripheral, cranial nerve paralysis, demyelinating polyneuropathy, Horner’s syndrome, polyneuropathy, and sciatica.
dDizziness includes dizziness, presyncope, and syncope.
eDyspnea includes dyspnea, dyspnea exertional, respiratory distress, and respiratory failure.

Other clinically important adverse reactions which occurred in <10% of patients include the following:

Blood and lymphatic system disorders: pancytopenia (3%), hemophagocytic lymphohistiocytosis (2%), B-cell aplasia (1%)

Cardiac disorders: cardiac failure (1%)

Eye disorders: visual impairment (6%)

Gastrointestinal disorders: vomiting (9%), stomatitis (6%), dry mouth (5%), abdominal distension (4%), ascites (3%)

General disorders and administration site conditions: influenza-like illness (9%), asthenia (7%), multiple organ dysfunction syndrome (3%)

Immune system disorders: infusion related reaction (3%)

Investigations: fibrin D dimer increased (4%)

Metabolism and nutrition disorders: hypocalcemia (5%), hypercalcemia (4%), hyperferritinemia (4%), tumor lysis syndrome (2%)

Musculoskeletal and connective tissue disorders: myalgia (5%)

Nervous system disorders: motor dysfunction (6%), tremor (6%), speech disorder (4%), neuralgia (3%), seizure (3%), ataxia (2%), ischemic cerebral infarction (1%)

Psychiatric disorders: delirium (5%)

Respiratory, thoracic, and mediastinal disorders: hypoxia (8%), oropharyngeal pain (8%), pleural effusion (5%), nasal congestion (4%), pulmonary edema (3%), tachypnea (3%)

Skin and subcutaneous tissue disorders: night sweats (5%), pruritus (4%), hyperhidrosis (4%), erythema (2%)

Vascular disorders: thrombosis (6%), hypertension (4%), capillary leak syndrome (1%)

Laboratory Abnormalities

Table 7. Grade 3 or 4 Laboratory Abnormalities Occurring in > 10% of Adult r/r DLBCL Patients in Study 2 (N = 115)
Laboratory parameter | Grade 3 or 4a (%)
Hematology
Lymphopenia | 95
Neutropenia | 82
Leukopenia | 78
Anemia | 59
Thrombocytopenia | 56
Biochemistry
Hypophosphatemia | 24
Hypokalemia | 13
aCTCAE = Common Terminology Criteria for Adverse Events version 4.03.

Adult r/r Follicular Lymphoma (FL)

The safety of KYMRIAH was evaluated in Study 3, a trial that included 97 patients with r/r FL who received a single intravenous dose of KYMRIAH [see Clinical Studies (14.3)]. Patients with a history of CNS disorders or autoimmune disease requiring systemic immunosuppression were ineligible. The median age was 57 years (range, 29 to 73 years), 34% were female, 75% were White, 13% were Asian, and 1% were Black or African American.

The most common adverse reactions (incidence > 20%) were CRS, infections-pathogen unspecified, fatigue, musculoskeletal pain, headache, and diarrhea.

The adverse reactions with greater than or equal to 10% incidence for any Grade are summarized in Table 8 below.

Table 8. Adverse Reactions Reported in ≥ 10% of Adult Patients with r/r FL in Study 3 (N = 97)
Adverse reaction | All Grades (%) | Grades 3 or higher (%)
Blood and lymphatic system disorders
Febrile neutropenia | 13 | 13
Gastrointestinal disorders
Diarrhea | 24 | 2
Nausea | 16 | 2
Constipation | 16 | 0
Abdominal paina | 10 | 1
General disorders and administration site conditions
Fatiguea | 27 | 3
Fever | 19 | 1
Immune system disorders
Cytokine release syndrome | 53 | 0
Hypogammaglobulinemiaa | 18 | 1
Infections and infestations
Infections-pathogen unspecified | 38 | 12
Viral infectious disordersb | 18 | 5
Musculoskeletal and connective tissue disorders
Musculoskeletal paina | 25 | 1
Arthralgia | 10 | 0
Nervous system disorders
Headachea | 25 | 2
Respiratory, thoracic and mediastinal disorders
Cougha | 19 | 0
Skin and subcutaneous tissue disorders
Rasha | 10 | 0
aIncludes multiple related composite terms.
bIncludes one case of progressive multifocal leukoencephalopathy due to John Cunningham virus reactivation.

Other clinically important adverse reactions which occurred in <10% of patients include the following:

Blood and lymphatic system disorders: pancytopenia (3%), hemolysis (2%), coagulopathy (2%)

Cardiac disorders: tachycardia (2%), arrhythmia (4%)

Eye disorders: visual impairment, blindness (preexisting progressive blindness, which initiated prior to start of lymphodepleting chemotherapy, further worsened after KYMRIAH infusion), vision blurred (4%)

Gastrointestinal disorders: vomiting (9%), stomatitis (4%), abdominal distension (2%), dry mouth (2%)

General disorders and administration site conditions: edema (9%), pain (8%), chills (6%)

Immune system disorders: infusion related reaction (3%), graft versus host disease (1%), hemophagocytic lymphohistiocytosis (1%)

Infections and infestations: bacterial infectious disorders (7%), fungal infectious disorders (2%)

Investigations: weight decreased (7%)

Metabolism and nutrition disorders: decreased appetite (8%), tumor lysis syndrome (2%)

Nervous system disorders: dizziness (8%), motor dysfunction (9%), peripheral neuropathy (7%), immune effector cell-associated neurotoxicity syndrome (4%), encephalopathy (3%), tremor (3%)

Psychiatric disorders: sleep disorder (6%), anxiety (2%), delirium (1%)

Renal and urinary disorder: acute kidney injury (4%)

Respiratory, thoracic, and mediastinal disorders: dyspnea (8%), pleural effusion (6%), oropharyngeal pain (5%), nasal congestion (2%), rhinorrhea (2%)

Skin and subcutaneous tissue disorders: pruritus (9%), night sweats (3%), erythema (2%), hyperhidrosis (1%)

Vascular disorders: hypotension (9%), hemorrhage (6%), hypertension (5%), thrombosis (1%)

Laboratory Abnormalities

Table 9. Grade 3 or 4 Laboratory Abnormalities Occurring in > 10% of Adult Patients with r/r FL Patients in Study 3 (N = 97*)
Laboratory abnormality | Grade 3 or 4a (%)
Hematology
Neutropenia | 63
Leukopenia | 40
Thrombocytopenia | 21
Anemia | 20
Lymphopenia | 19
Biochemistry
Hypophosphatemia | 12
aCTCAE = Common Terminology Criteria for Adverse Events version 4.03.
*Evaluable population (n = 91 to 97) for each laboratory value included number of patients who had both baseline (before KYMRIAH infusion) and at least one post-KYMRIAH infusion on-study laboratory value available.

6.2 Postmarketing Experience

Because adverse events to marketed products are reported voluntarily from a population of uncertain size, it is not always possible to reliably estimate their frequency or establish a causal relationship to product exposure.

The following adverse events have been identified during postmarketing use of KYMRIAH.

- Immune system disorders: Anaphylactic reaction
- Neoplasms: T cell malignancies
- Infections and infestations: Progressive multifocal leukoencephalopathy
- Eye disorders: Blindness

7 DRUG INTERACTIONS

HIV and the lentivirus used to make KYMRIAH have limited, short spans of identical genetic material (RNA). Therefore, some commercial HIV nucleic acid tests (NATs) may yield false-positive results in patients who have received KYMRIAH.

8 USE IN SPECIFIC POPULATIONS

8.1 Pregnancy

Risk Summary

There are no available data with KYMRIAH use in pregnant women. No animal reproductive and developmental toxicity studies have been conducted with KYMRIAH to assess whether it can cause fetal harm when administered to a pregnant woman. It is not known if KYMRIAH has the potential to be transferred to the fetus. Based on the mechanism of action, if the transduced cells cross the placenta, they may cause fetal toxicity, including B-cell lymphocytopenia. Therefore, KYMRIAH is not recommended for women who are pregnant, and pregnancy after KYMRIAH administration should be discussed with the treating physician. Report pregnancies to Novartis Pharmaceuticals Corporation at 1-888-669-6682.

In the U.S. general population, the estimated background risk of major birth defects and miscarriage in clinically recognized pregnancies is 2% to 4% and 15% to 20%, respectively.

8.2 Lactation

Risk Summary

There is no information regarding the presence of KYMRIAH in human milk, the effect on the breastfed infant, and the effects on milk production. A risk to the breastfed infant cannot be excluded. The developmental and health benefits of breastfeeding should be considered along with the mother’s clinical need for KYMRIAH and any potential adverse effects on the breastfed infant from KYMRIAH or from the underlying maternal condition.

8.3 Females and Males of Reproductive Potential

Pregnancy Testing

Pregnancy status of females with reproductive potential should be verified. Sexually active females of reproductive potential should have a pregnancy test prior to starting treatment with KYMRIAH.

Contraception

See the prescribing information for fludarabine and cyclophosphamide for information on the need for effective contraception in patients who receive the lymphodepleting chemotherapy.

There are insufficient exposure data to provide a recommendation concerning duration of contraception following treatment with KYMRIAH.

Infertility

There are no data on the effect of KYMRIAH on male and female fertility.

8.4 Pediatric Use

The safety and efficacy of KYMRIAH have been established in pediatric patients with r/r B-cell ALL. Use of KYMRIAH is supported by a single-arm trial [see Clinical Studies (14.1)] that included 61 pediatric patients with r/r B-cell precursor ALL in the following age groups: 40 children (ages 2 years to less than 12 years) and 21 adolescents (ages 12 years to less than 17 years). No differences in efficacy or safety were observed between the different age subgroups or in comparison to the young adults in the trial.

The safety and efficacy of KYMRIAH in pediatric patients with r/r DLBCL and r/r FL have not been established.

8.5 Geriatric Use

The safety and effectiveness of KYMRIAH have not been established in geriatric patients with r/r B-cell ALL. Clinical studies of KYMRIAH did not include sufficient numbers of subjects aged 65 and over to determine whether they respond differently from younger subjects.

11 DESCRIPTION

KYMRIAH (tisagenlecleucel) is a CD19-directed genetically modified autologous T cell immunotherapy comprised of autologous T cells that are genetically modified using a lentiviral vector to encode an anti-CD19 chimeric antigen receptor (CAR). The CAR is comprised of a murine single-chain antibody fragment (scFv) specific for CD19, followed by a CD8 hinge and transmembrane region that is fused to the intracellular signaling domains for 4-1BB (CD137) and CD3 zeta.

KYMRIAH is prepared from the patient’s peripheral blood mononuclear cells, which are obtained via a standard leukapheresis procedure. The mononuclear cells are enriched for T cells, then transduced with the lentiviral vector containing the anti-CD19 CAR transgene and activated with anti-CD3/CD28 antibody coated beads. The transduced T cells are expanded in cell culture, washed, and formulated into a suspension, which then is cryopreserved. The product must pass a sterility test before release for shipping as a frozen suspension in a patient-specific infusion bag(s). The product is thawed prior to administration [see Dosage and Administration (2.2), How Supplied/Storage and Handling (16)]. The thawed product is a colorless to slightly yellow suspension of cells.

In addition to T cells, other cell populations, including monocytes, NK cells, and B cells, may be present. The formulation contains 31.25% (v/v) of Plasma-Lyte A, 31.25% (v/v) of 5% Dextrose/0.45% sodium chloride, 10% Dextran 40 (LMD)/5% Dextrose, 20% (v/v) of 25% Human Serum Albumin (HSA), and 7.5% (v/v) dimethyl sulfoxide (DMSO).

Pediatric and Young Adult r/r B-cell ALL: A single dose of KYMRIAH may contain up to 2.5 x 10^8 CAR-positive viable T cells provided in one to three patient-specific infusion bag(s). Based on the patient’s weight reported at the time of leukapheresis, one of two possible dose ranges will be prepared for the patient:

- For patients 50 kg or less: 0.2 to 5.0 x 10^6 CAR-positive viable T cells per kg body weight.
- For patients above 50 kg: 0.1 to 2.5 x 10^8 CAR-positive viable T cells.

Adult r/r DLBCL and r/r FL: A single dose of KYMRIAH may contain 0.6 to 6.0 x 10^8 CAR-positive viable T cells provided in one to three patient-specific infusion bag(s).

The actual number of CAR-positive T cells in the product is reported on the Certificate of Analysis (CoA) that is shipped with KYMRIAH. The volume of CAR-positive viable T cells in an infusion bag ranges from 10 mL to 50 mL.

12 CLINICAL PHARMACOLOGY

12.1 Mechanism of Action

KYMRIAH is a CD19-directed genetically modified autologous T cell immunotherapy which involves reprogramming a patient’s own T cells with a transgene encoding a chimeric antigen receptor (CAR) to identify and eliminate CD19-expressing malignant and normal cells. The CAR is comprised of a murine single-chain antibody fragment which recognizes CD19 and is fused to intracellular signaling domains from 4-1BB (CD137) and CD3 zeta. The CD3 zeta component is critical for initiating T cell activation and antitumor activity, while 4-1BB enhances the expansion and persistence of KYMRIAH. Upon binding to CD19-expressing cells, the CAR transmits a signal to promote T cell expansion, activation, target cell elimination, and persistence of the KYMRIAH cells.

12.2 Pharmacodynamics

Due to the on-target effect of KYMRIAH, a period of B-cell aplasia is expected.

Among evaluable pediatric and young adult r/r B-cell ALL patients with an ongoing response at Month 24, 33% had no detectable B cells at baseline prior to infusion. At Month 24, 88% had no detectable B cells.

Most adult r/r DLBCL patients had B-cell depletion at baseline prior to infusion due to previous treatment with rituximab. Recovery of B-cell levels were observed with longer follow-up in some of the responding DLBCL patients after KYMRIAH infusion. Among evaluable adult r/r DLBCL and FL patients with an ongoing response at Month 24, all patients had no detectable B cells at baseline prior to infusion or at Month 24.

12.3 Pharmacokinetics/Cellular Kinetics

Following infusion, KYMRIAH exhibited an initial rapid expansion followed by a bi-exponential decline in pediatric and young adult r/r B-cell acute lymphoblastic leukemia (ALL) patients, adult r/r diffuse large B-cell lymphoma patients, and adult r/r follicular lymphoma patients.

A summary of pharmacokinetic parameters of KYMRIAH is provided in Table 10 below.

Table 10. Pharmacokinetic Parameters of KYMRIAH in Pediatric and Young Adult r/r B-cell ALL, Adult r/r DLBCL, and Adult r/r FL
Parameter | Summary statistics | Pediatric ALL responding patients N = 62 | Pediatric ALL non-responding patients N = 8 | r/r DLBCL responding patients (CR and PR) N = 34 | r/r DLBCL non- responding patients (SD/PD/ unknown) N = 34 | r/r FL responding patients (CR and PR) N = 77 | r/r FL non-responding patients (SD/PD) N = 12
Cmax (copies/mcg) | Geometric mean (CV%), n | 34,700 (155.4), 61 | 20,000 (71.6), 7 | 5,210 (256.5), 33 | 6,450 (408.2), 32 | 6,250 (344), 64 | 3,000 (1190), 8
Tmax (day) | Median [min; max], n | 9.91 [0.008; 27], 61 | 20.0 [0.03; 62.7], 7 | 9.83 [5.73; 16.8], 33 | 8.39 [3.04; 27.7], 32 | 9.94 [2.62; 28.0], 64 | 13.0 [7.73; 16.0], 8
AUC0-28d (copies/mcg*day) | Geometric mean (CV%), n | 318,000 (177.8), 61 | 156,000 (99.4), 6 | 58,200 (165.1), 30 | 75,800 (292.3), 25 | 56,900 (270), 63 | 20,100 (18100), 7
T½ (day) | Geometric mean (CV%), n | 16.8 (155.9), 54 | 2.52 (171.9), 3 | 45.3 (157.7), 21 | 13.6 (167.0), 22 | 44.0 (296), 42 | 24.4 (180), 6

Description of Pharmacokinetics in Pediatric and Young Adult r/r B-cell ALL (up to 25 years of age)

The Cmax and AUC0-28d were similar between CR/CRi patients compared with non-responding (NR) patients.

KYMRIAH was present in the blood as well as bone marrow and was measurable beyond 2 years. Blood to bone marrow partitioning suggested that KYMRIAH distribution in bone marrow was 44% of that present in blood at Day 28 while at Months 3 and 6 KYMRIAH distributed at 67% and 69%, respectively, indicating high distribution to bone marrow.

Children < 10 years and between 10-18 years of age had similar- to 1.7-fold higher Cmax and AUC0-28d than adults. Due to small sample size and high variability, it is difficult to assess the impact of age on the pharmacokinetics of KYMRIAH.

Description of Pharmacokinetics in Adult r/r DLBCL

The Cmax and AUC0-28d were similar between responding and non-responding (NR) patients.

KYMRIAH was present in adult r/r DLBCL patients up to 18 months in peripheral blood and up to 9 months in the bone marrow for patients having a complete response (CR). The median time of maximal expansion of transgene levels (Tmax) in peripheral blood occurred at 9-10 days in both responding and non-responding patients.

Description of Pharmacokinetics in Adult r/r FL

KYMRIAH has been detected for up to 18 months in peripheral blood and up to 3 months in bone marrow for patients who achieved a response. The median time of maximal expansion of transgene levels (Tmax) in peripheral blood occurred at 10 days in responding and 13 days in non-responding patients.

The blood to bone marrow partitioning in bone marrow was nearly 50% at Month 3 in responding patients.

The geometric mean AUC0-28d value of responders was 183% higher compared to non-responders, while the geometric mean Cmax value was 108% higher in responders compared to non-responders. Considering the high inter-individual variability, small number of non-responders, overlapping expansion ranges observed between responders and non-responders, the exposure differences should be interpreted with caution.

Tocilizumab and Corticosteroid used for CRS Management

Some patients required tocilizumab and corticosteroids for the management of CRS. KYMRIAH continues to expand and persist following treatment as per the CRS management algorithm (see Table 1). Patients who have higher expansion tended to have higher CRS Grades [see Warnings and Precautions (5.1)].

Pediatric and young adult r/r B-cell ALL patients (N = 28) treated with tocilizumab had 298% and 183% higher KYMRIAH AUC0-28d and Cmax, respectively, as compared to patients (N = 46) who did not receive tocilizumab. In addition, patients who received corticosteroids for CRS management (N = 17) had 280% higher AUC0-28d compared with patients who did not receive corticosteroids (N = 31).

Adult r/r DLBCL patients treated with tocilizumab (N = 18) had 238% (n = 14) and 311% (n = 16) higher KYMRIAH AUC0-28d and Cmax, respectively, as compared to patients (N = 97) who did not receive tocilizumab. In addition, patients who received corticosteroids for CRS management (N = 12) had 104% and 179% higher AUC0-28d and Cmax, respectively, as compared with patients who did not receive corticosteroids (N = 79).

Adult r/r FL patients treated with tocilizumab (N = 14) had 245% (n = 12) and 312% (n = 11) higher KYMRIAH AUC0-28d and Cmax, respectively, as compared to patients (N = 76) who did not receive tocilizumab. Three patients received corticosteroids for CRS management while all other patients received corticosteroids for other reasons, therefore a formal comparison for exposure differences by use of corticosteroids cannot be performed.

Hepatic and renal impairment studies of KYMRIAH were not conducted.

12.6 Immunogenicity

The observed incidence of anti-drug antibodies is highly dependent on the sensitivity and specificity of the assay. Differences in assay methods preclude meaningful comparisons of the incidence of anti-product antibodies in the studies described below with the incidence of anti-product antibodies in other studies, including those of KYMRIAH or of other similar products.

In clinical studies, humoral immunogenicity of KYMRIAH was measured by determination of anti-murine CAR19 antibodies (anti-mCAR19) in serum pre- and post-administration. The majority of patients, 91% in Study 1, 94% in Study 2, and 66% in Study 3, tested positive for pre-dose anti-mCAR19 antibodies prior to KYMRIAH infusion. Treatment induced anti-mCAR19 antibodies were detected in 9% and 33% of the patients in Study 2 and Study 3, respectively. However, the preexisting and treatment-induced antibodies were not associated with an impact on clinical response and did not have an impact on the initial expansion and persistence of KYMRIAH. Persistence of KYMRIAH was similar between patients with positive post-infusion anti-mCAR19 antibodies compared with patients with negative post-infusion anti-mCAR19 antibodies. There is no evidence that the presence of preexisting and treatment-induced anti-mCAR19 antibodies impact the safety or effectiveness of KYMRIAH.

T cell immunogenicity responses were not observed in r/r ALL, r/r DLBCL, or r/r FL patients.

13 NONCLINICAL TOXICOLOGY

13.1 Carcinogenesis, Mutagenesis, Impairment of Fertility

Genotoxicity assays and carcinogenicity assessment in rodent models were not performed for KYMRIAH. In vitro expansion studies with transduced T cells (KYMRIAH) from healthy donors and patients showed no evidence for transformation and/or immortalization of T cells. In vivo studies in immunocompromised mice did not show signs of abnormal cell growth or signs of clonal cell expansion for up to 7 months after cell injection. A genomic insertion site analysis was performed on KYMRIAH products from 14 individual donors (12 patients and 2 healthy volunteers). There was no evidence for preferential integration near genes of concern, or preferential outgrowth of cells harboring integration sites of concern.

No studies on the effects of KYMRIAH on fertility have been conducted.

14 CLINICAL STUDIES

14.1 Relapsed or Refractory B-cell Acute Lymphoblastic Leukemia

The efficacy of KYMRIAH in pediatric and young adults with r/r B-cell precursor ALL was evaluated in an open-label, multicenter single-arm trial (Study 1: CCTL019B2202; NCT02435849). In total, 107 patients were screened, 88 were enrolled, 68 were treated, and 63 were evaluable for efficacy. Nine percent of the enrolled patients did not receive the product due to manufacturing failure. The 63 evaluable patients included 35 males and 28 females of median age 12 years (range, 3 to 23 years). Seventy-three percent of patients were White, 10% were Asian, and 17% were of other races. Six (10%) had primary refractory disease, 30 (48%) had one prior stem cell transplantation, 5 patients (8%) had two stem cell transplantations. Treatment consisted of lymphodepleting chemotherapy (fludarabine 30 mg/m^2 daily for 4 days and cyclophosphamide 500 mg/m^2 daily for 2 days) followed by a single dose of KYMRIAH. Of the 22 patients who had a WBC count < 1000/µL, 20 received lymphodepleting chemotherapy prior to KYMRIAH while 2 received KYMRIAH infusion without lymphodepleting chemotherapy. Fifty-three patients received bridging chemotherapy between time of enrollment and lymphodepleting chemotherapy.

The efficacy of KYMRIAH was established on the basis of complete remission (CR) within 3 months after infusion, the duration of CR, and proportion of patients with CR and minimal residual disease (MRD) < 0.01% by flow cytometry (MRD-negative) (Table 11). Among the 63 infused patients, 52 (83%) achieved CR/CRi, all of which were MRD-negative. With a median follow-up of 4.8 months from response, the median duration of CR/CRi was not reached (range, 1.2 to 14.1+ months). Median time to onset of CR/CRi was 29 days with onset of CR/CRi between 26 and 31 days for 50/52 (96%) responders. The stem cell transplantation rate among those who achieved CR/CRi was 12% (6/52). Table 11 shows the efficacy results from this study.

Table 11. Efficacy Results in Pediatric and Young Adult Patients with r/r B-cell ALL
Results | N = 63
CR/CRi^1,2 (95% CI) | 52 (83%) (71%, 91%) p < 0.0001
CR^3 | 40 (63%)
CRi^4 | 12 (19%)
CR or CRi with MRD-negative bone marrow^5,6 (95% CI) | 52 (83%) (71%, 91%) p < 0.0001
Duration of remission^7 | N = 52
Median (months) | Not reached
(95% CI) | (7.5, NE^8)
^1CR/CRi was calculated based on all patients who received KYMRIAH and completed at least 3 months follow-up or discontinued earlier prior to the data cut-off. Requires remission status to be maintained for at least 28 days without clinical evidence of relapse.
^2The null hypothesis of CR/CRi less than or equal to 20% was rejected.
^3CR (complete remission) was defined as less than 5% of blasts in the bone marrow, no evidence of extramedullary disease, and full recovery of peripheral blood counts (platelets greater than 100,000/microliter and absolute neutrophil counts [ANC] greater than 1,000/microliter) without blood transfusion.
^4CRi (complete remission with incomplete blood count recovery) was defined as less than 5% of blasts in the bone marrow, no evidence of extramedullary disease, and without full recovery of peripheral blood counts with or without blood transfusion.
^5MRD (minimal residual disease) negative was defined as MRD by flow cytometry less than 0.01%.
^6The null hypothesis of MRD-negative remission rate less than or equal to 15% was rejected.
^7DOR (duration of remission) was defined as time since onset of CR or CRi to relapse or death due to underlying cancer, whichever is earlier, censoring for new cancer therapy including stem cell transplantation (N = 52).
^8Not Estimable.

14.2 Adult Relapsed or Refractory Diffuse Large B-cell Lymphoma

The efficacy and safety of KYMRIAH was evaluated in an open-label, multicenter, single-arm trial (Study 2: CCTL019C2201; NCT02445248). Eligible patients were ≥ 18 years of age with relapsed or refractory DLBCL, who received ≥ 2 lines of chemotherapy, including rituximab and anthracycline, or relapsed following autologous hematopoietic stem cell transplantation (HSCT). The study excluded patients with active central nervous system malignancy, prior allogenic HSCT, an ECOG performance status ≥ 2, a creatinine clearance < 60, alanine aminotransferase > 5 times normal, cardiac ejection fraction < 45%, or absolute lymphocyte concentration less than 300/µL.

Following 2 to 11 days after completion of lymphodepleting (LD) chemotherapy consisting of either fludarabine (25 mg/m^2 intravenously daily for 3 days) and cyclophosphamide (250 mg/m^2 intravenously daily for 3 days starting with the first dose of fludarabine) or bendamustine (90 mg/m^2 intravenously daily for 2 days), KYMRIAH was administered as a single intravenous infusion. Bridging chemotherapy between leukapheresis and LD chemotherapy was permitted to control disease burden. LD chemotherapy could be omitted if the white blood cell count was < 1000 cells/µL. The major efficacy outcome measures were objective response rate per Lugano criteria [2014] as assessed by an independent review committee and duration of response.

Of the 160 patients enrolled, 106 patients received tisagenlecleucel, including 92 patients who received product manufactured in the U.S. and were followed for at least 3 months or discontinued earlier. Eleven out of 160 patients enrolled did not receive tisagenlecleucel due to manufacturing failure. Thirty-eight other patients did not receive tisagenlecleucel, primarily due to death (n = 16), physician decision (n = 16), and adverse events (n = 3).

Of the 92 patients receiving KYMRIAH, 90% received physician’s choice of bridging chemotherapy in the interval between start of screening and KYMRIAH infusion, among whom the median number of bridging chemotherapy regimens was 1 (range, 1 to 5) with 83% of patients receiving ≤ 2 regimens. A retrospectively identified sub-group of 68 patients was evaluable for the major efficacy outcome measures. Patients included in this sub-group had either had no bridging chemotherapy, or had imaging that showed measurable disease after completion of bridging chemotherapy, prior to KYMRIAH infusion. Of the 24 patients not included, 8 had no evidence of disease at baseline prior to KYMRIAH infusion, 15 did not have baseline imaging following bridging chemotherapy, and 1 was excluded because of initial misclassification of a neuroendocrine tumor as DLBCL.

Among the efficacy evaluable population of 68 patients, the baseline characteristics were median age 56 years (range, 22 to 74 years); 71% male; 90% White, 4% Asian, and 3% Black or African American; 78% had primary DLBCL not otherwise specified (NOS) and 22% had DLBCL following transformation from follicular lymphoma, of whom 17% were identified as high grade; and 44% had undergone prior autologous HSCT. The median number of prior therapies was 3 (range, 1 to 6), 56% had refractory disease and 44% relapsed after their last therapy. Ninety percent of patients received lymphodepleting chemotherapy (66% of patients received fludarabine and 24% received bendamustine) and 10% did not receive any LD chemotherapy. The median time from leukapheresis and cryopreservation to KYMRIAH infusion was 113 days (range, 47 to 196 days). The median dose was 3.5 × 10^8 CAR-positive viable T cells (range, 1.0 to 5.2 × 10^8 cells). Seventy-three percent of patients received KYMRIAH in the inpatient setting.

Efficacy was established on the basis of CR rate and duration of response (DOR), as determined by an independent review committee (Table 12 and Table 13). The median time to first response to KYMRIAH (CR or PR) was 0.9 months (range, 0.7 to 3.3 months). The median duration of response was not reached. Response durations were longer in patients who achieved CR, as compared to patients with a best response of partial response (PR) (Table 13). Of the 22 patients who experienced a CR, 9 achieved this status by 1 month, 12 more by month 3, and the last by month 6 after KYMRIAH infusion.

Table 12. Response Rates in Relapsed or Refractory DLBCL in the JULIET Study
Response rate | N = 68
Overall response rate (ORR) (CR+PR), n (%) (95% CI) Complete response rate n (%) (95% CI) Partial response rate n (%) (95% CI) | 34 (50%) (37.6%, 62.4%) 22 (32%) (21.5%, 44.8%) 12 (18%) (9.5%, 28.8%)

Table 13. Duration of Responsea (Months) in Relapsed or Refractory DLBCL in the JULIET Study
Duration of response | Results
Overall DOR for responders (months) | N = 34
Median DORa,b | NE
(95% CI) | (5.1, NE)
Rangec | (0.03+ – 11.3+)
Median Follow-up (95% CI)b | 9.4 (7.9, 10.8)
DOR if BOR is CR | N = 22
Median DORa,b | NE
(95% CI) | (10.0, NE)
Rangec | (1.5+ – 11.3+)
DOR if BOR is PR | N = 12
Median DORa,b | 3.4
(95% CI) | (1.0, NE)
Rangec | (0.03+ – 11.3+)
Abbreviations: CR, Complete Response; DOR, Duration of Response; NE, not estimable; PR, partial response.
aAmong all responders. DOR measured from date of first objective response to date of progression or death from relapse.
bKaplan-Meier estimate in months.
cA + sign indicates a censored value.

14.3 Adult Relapsed or Refractory Follicular Lymphoma

The efficacy of KYMRIAH was evaluated in a multicenter, single-arm, open-label trial (Study 3: CCTL019E2202; NCT03568461) that included patients who were refractory to or relapsed within 6 months after completion of two or more lines of systemic therapy (including an anti-CD20 antibody and an alkylating agent), relapsed during or within six months after completion of an anti-CD20 antibody maintenance therapy following at least two lines of therapy, or relapsed after autologous hematopoietic stem cell transplant (HSCT). The trial excluded patients with active or serious infections, transformed lymphoma, or other aggressive lymphomas, prior allogeneic HSCT, or disease with active CNS involvement. Following lymphodepleting (LD) chemotherapy, KYMRIAH was administered as a single dose intravenous infusion with a target dose of 0.6 to 6.0 × 10^8 CAR-positive viable T cells. The median dose administered was 2.06 × 10^8 CAR-positive viable T cells (range, 0.1 to 6.0 × 10^8 CAR-positive viable T cells). The LD chemotherapy regimen consisted of either fludarabine (25 mg/m^2 intravenously daily for 3 days) and cyclophosphamide (250 mg/m^2 intravenously daily for 3 days starting with the first dose of fludarabine) or bendamustine (90 mg/m^2 IV daily for 2 days); bridging chemotherapy between leukapheresis and LD chemotherapy was permitted as needed. Of the 90 patients included in the primary efficacy analysis, 40 patients (45%) were treated with bridging therapies. The most commonly used agents (in ≥ 5% of patients) were rituximab (22%), dexamethasone (13%), gemcitabine (12%), prednisone (11%), oxaliplatin (8%), etoposide (8%), and vincristine (6%).

Of 98 patients who were enrolled and underwent leukapheresis, 97 patients received infusion with KYMRIAH and one patient without measurable disease did not receive KYMRIAH. There were no manufacturing failures for the 98 enrolled patients. Of the 97 patients infused with KYMRIAH, the efficacy evaluable population, as specified in the protocol, included the first 90 patients with measurable disease who received KYMRIAH consecutively and had at least 9 months follow-up from first objective response or discontinued earlier.

Among the 90 patients with FL included in the efficacy analysis, the median age was 58 years (range, 29 to 73 years), 31% were female, 78% were White, 10% were Asian, and 1% were Black or African American. The median number of prior therapies was 4 (range, 2 to 13), with 24% receiving 2 prior lines, 21% receiving 3 prior lines, and 54% receiving ≥4 prior lines. Eighty-seven percent had Stage III-IV disease at study entry, 64% had bulky disease, 36% had a prior autologous HSCT, 79% were refractory to the most recent regimen, and 66% had progression within 24 months of initiating their first anti-CD20 combination therapy (POD24).

Efficacy was established on the basis of objective response rate and duration of response (DOR) as determined by an independent review committee (Table 14 and Table 15). The first disease assessment was scheduled to be performed at Month 3 post-infusion; the median time to first response was 2.9 months (range, 0.6 to 6.0 months). All responders achieved their response (complete response [CR] or partial response [PR]) at the first performed post-infusion disease assessment.

Table 14. Response Rates in Patients with Relapsed or Refractory FL
Response | Primary efficacy population N = 90 | All leukapheresed patients N = 98
Overall response rate (ORR), n (%) (95% CI) | 77 (86%) (76.6, 92.1) | 84 (86%) (77.2, 92.0)
Complete response rate (CRR)a,b, n (%) (95% CI) | 61 (68%) (57.1, 77.2) | 66 (67%) (57.1, 76.5)
aTwo patients, included in the Primary Efficacy Population, with best overall response of CR, had their disease relapsed more than 6 months after the last line of therapy.
bOf the 30 patients who initially achieved a PR, 14 patients (47%) converted to a CR, including 10 patients at the next subsequent visit and within 6 months post-infusion.

Table 15. Duration of Response in Patients with Relapsed or Refractory FL
 | From N = 90
Overall DOR, months | N = 77
Median (95% CI)a,b | NE (15.6, NE)
Rangec | (0.03+, 21.1+)
Median Follow-up | 9.1*
% event-free probability
At 9 months (95% CI) | 75.2 (63.5, 83.6)
At 12 months (95% CI) | 70.8 (58.0, 80.3)
DOR if best response is CR, months | N = 61
Median (95% CI)a,b | NE (15.6, NE)
Rangec | (2.7, 21.1+)
% event-free probability
At 9 months (95% CI) | 87.7 (75.8, 93.9)
At 12 months (95% CI) | 85.2 (72.2, 92.4)
Abbreviations: CR, complete response; DOR, duration of response; NE, not estimable.
*The first disease assessment was scheduled to be performed at Month 3 post-infusion. The median follow up is the time from first objective response to last disease assessment.
aAmong responders. DOR measured from date of first objective response to date of progression or death from relapse.
bKaplan-Meier estimate in months.
cA + sign indicates a censored value.

15 REFERENCES

1. Porter DL, Hwang WT, Frey N, et al. (2015). Chimeric antigen receptor T cells persist and induce sustained remissions in relapsed refractory chronic lymphocytic leukemia (Table S4A). Sci. Transl Med; 7(303):303ra139. DOI: 10.1126/scitranslmed.aac5415.

2. Lee DW, Gardner R, Porter DL, et al. (2014). Current concepts in the diagnosis and management of cytokine release syndrome. Blood; 124(2):188-95.

3. Lee DW, Santomasso BD, Locke FL, et al. (2019) ASTCT Consensus Grading for Cytokine Release Syndrome and Neurologic Toxicity Associated with Immune Effector Cells. Biol Blood Marrow Transplant; 25(4):625-38.

4. Santomosso BD, Nastoupil LJ, Adkins S, et al. (2021) Management of Immune-Related Adverse Events in Patients Treated With Chimeric Antigen Receptor T-Cell Therapy: ASCO Guideline. J Clin Oncol; 39(35):3978-92.

16 HOW SUPPLIED/STORAGE AND HANDLING

KYMRIAH is supplied as a frozen suspension of genetically modified autologous T cells in an infusion bag(s) labeled for the specific recipient. KYMRIAH is shipped directly to the cell lab associated with the infusion center in a liquid nitrogen Dewar. Product and patient-specific labels are located inside the Dewar.

Ped ALL: NDC 0078-0846-19

DLBCL and FL: NDC 0078-0958-19

- Confirm patient identity upon receipt.
- Store infusion bag(s) in a temperature-monitored system less than or equal to minus 120°C, e.g., in the vapor phase of liquid nitrogen.
- Use closed, break-proof, leak-proof containers when transporting infusion bags within the facility.
- Thaw KYMRIAH prior to infusion [see Dosage and Administration (2)].

17 PATIENT COUNSELING INFORMATION

Advise the patient to read the FDA-approved patient labeling (Medication Guide).

Ensure that patients understand the risk of manufacturing failure. This has been reported in up to 9% of manufacturing attempts. In case of a manufacturing failure, a second manufacturing of KYMRIAH may be attempted. In addition, while the patient awaits the product, additional chemotherapy (not the lymphodepletion) may be necessary and may increase the risk of adverse events during the pre-infusion period.

Prior to infusion, advise patients of the following risks:

- Cytokine Release Syndrome (CRS) -- Report signs and symptoms of CRS (high fever, difficulty breathing, chills/shaking chills, severe nausea, severe vomiting, severe diarrhea, severe muscle pain, severe joint pain, very low blood pressure, or dizziness/lightheadedness) to their healthcare professional [see Warnings and Precautions (5.1), Adverse Reactions (6.1)].
- Neurological Toxicities -- Report altered or decreased consciousness, delirium, confusion, agitation, seizures, difficulty speaking and understanding, or loss of balance to their healthcare professional. Avoid driving for at least 2 weeks after KYMRIAH administration [see Warnings and Precautions (5.2), Adverse Reactions (6.1)].
- Hemophagocytic Lymphohistiocytosis (HLH)/Macrophage Activation Syndrome (MAS) -- Presenting signs and symptoms are similar to those of CRS and infections [see Warnings and Precautions (5.3), Adverse Reactions (6.1)].
- Serious Infections -- KYMRIAH may cause serious infections. Advise patients that they will be screened for HBV, HCV, and HIV before collection of cells [see Warnings and Precautions (5.5), Adverse Reactions (6.1)].
- Hypogammaglobulinemia -- Patients may need to receive immunoglobulin replacement for an indefinite amount of time following treatment with KYMRIAH. Patients should tell their physician about their treatment with KYMRIAH before receiving a live vaccine [see Warnings and Precautions (5.7), Adverse Reactions (6.1)].
- Prolonged Cytopenia -- Patient may exhibit signs or symptoms associated with bone marrow suppression (i.e., neutropenia, thrombocytopenia and anemia) for several weeks following lymphodepleting chemotherapy and KYMRIAH [see Warnings and Precautions (5.6)].
- Secondary Malignancies -- Secondary malignancies, including T cell malignancies, have occurred [see Boxed Warning, Warnings and Precautions (5.8), Adverse Reactions (6.2)].

Patients should be instructed to contact Novartis Pharmaceuticals Corporation at 1-844-4KYMRIAH if they get secondary malignancies [see Warnings and Precautions (5.8)].

Distributed by:
Novartis Pharmaceuticals Corporation
East Hanover, New Jersey 07936
US License Number 1244

© Novartis

T2025-69

MEDICATION GUIDE
KYMRIAH® (pronounced KIM-RYE-AH)
(tisagenlecleucel)
suspension, for intravenous infusion

Read this Medication Guide before you start your KYMRIAH treatment. The more you know about your treatment, the more active you can be in your care. Talk with your healthcare provider if you have questions about your health condition or treatment. Reading this Medication Guide does not take the place of talking with your healthcare provider about your treatment.

What is the most important information I should know about KYMRIAH?
KYMRIAH may cause side effects that are severe or life-threatening. Call your healthcare provider or get emergency help right away if you get any of the following:

- difficulty breathing
- fever (100.4°F/38°C or higher)
- chills/shaking chills
- confusion
- severe nausea, vomiting, diarrhea
- severe muscle or joint pain
- very low blood pressure
- dizziness/lightheadedness

It is important that you tell your healthcare providers that you have received KYMRIAH. Your healthcare providers may give you other medicines to treat your side effects.

What is KYMRIAH?
KYMRIAH is made from your own white blood cells and is a prescription cancer treatment used in patients up to 25 years old who have acute lymphoblastic leukemia (ALL) that is either relapsing (went into remission, then came back) or refractory (did not go into remission after receiving other leukemia treatments). It is also used in patients with large B-cell lymphoma or follicular lymphoma, two types of non-Hodgkin lymphoma, that have relapsed or are refractory after having at least two other kinds of treatment.

How will I get KYMRIAH?
Since KYMRIAH is made from your own white blood cells, your healthcare provider has to take some of your blood. This is called “leukapheresis.” It takes 3 to 6 hours and may need to be repeated. A tube (intravenous catheter) will be placed in your vein to collect your blood.
Your blood cells are frozen and sent to the manufacturing site to make KYMRIAH. It takes about 3-4 weeks from the time your cells are received at the manufacturing site and shipped back to your healthcare provider, but the time may vary.
While waiting for KYMRIAH to be made, your healthcare provider may give you therapy to stabilize your cancer.
In addition, before you get KYMRIAH, your healthcare provider may give you chemotherapy for a few days to prepare your body.
When your body is ready, your healthcare provider will give you KYMRIAH through a tube (intravenous catheter) in your vein. This usually takes less than one hour.
You should plan to stay close to a healthcare facility for at least 2 weeks after getting KYMRIAH. Your healthcare provider will check to see if your treatment is working and help you with any side effects that occur.

What should I avoid after receiving KYMRIAH?

- Avoid driving for at least 2 weeks after you get KYMRIAH.
- Do not donate blood, organs, tissues, sperm, oocytes, and other cells.

What are the possible or reasonably likely side effects of KYMRIAH?
The most common side effects of KYMRIAH are:

- difficulty breathing
- fever (100.4°F/38°C or higher)
- chills/shaking chills
- confusion
- severe nausea, vomiting, diarrhea
- severe muscle or joint pain
- very low blood pressure
- dizziness/lightheadedness
- headache

KYMRIAH can increase the risk of life-threatening infections that may lead to death. Tell your healthcare provider right away if you develop fever, chills, or any signs or symptoms of an infection.
KYMRIAH can lower one or more types of your blood cells (red blood cells, white blood cells, or platelets). After treatment, your healthcare provider will test your blood to check for this. Tell your healthcare provider right away if you get a fever, are feeling tired, weak, or short of breath, or have bruising or bleeding.
Having KYMRIAH in your blood may cause a false-positive HIV test result by some commercial tests.
KYMRIAH may increase your risk of getting cancers, including certain types of blood cancers. Your healthcare provider should monitor you for this.
These are not all the possible side effects of KYMRIAH. Call your doctor for medical advice about side effects. You may report side effects to FDA at 1-800-FDA-1088.

General information about the safe and effective use of KYMRIAH.
Medicines are sometimes prescribed for purposes other than those listed in a Medication Guide.
Do not use KYMRIAH for a condition for which it was not prescribed.
Talk to your healthcare provider about any concerns. You can ask your healthcare provider for information about KYMRIAH that is written for healthcare professionals.
Distributed by:
Novartis Pharmaceuticals Corporation, East Hanover, New Jersey 07936.
US License Number 1244
© Novartis
For more information, go to KYMRIAH.com or call 1-888-669-6682.

This Medication Guide has been approved by the U.S. Food and Drug Administration.

Revised: June 2025

T2025-34

PRINCIPAL DISPLAY PANEL

tisagenlecleucel

KYMRIAH®

NDC 0078-0958-19

Human T cells

Rx only

Suspension for IV infusion

Cultured, genetically modified

For autologous use only

Dispense with Medication Guide

NOVARTIS

PRINCIPAL DISPLAY PANEL

tisagenlecleucel

KYMRIAH®

NDC 0078-0846-19

Human T cells

Rx only

Suspension for IV infusion

Cultured, genetically modified

For autologous use only

Dispense with Medication Guide

NOVARTIS